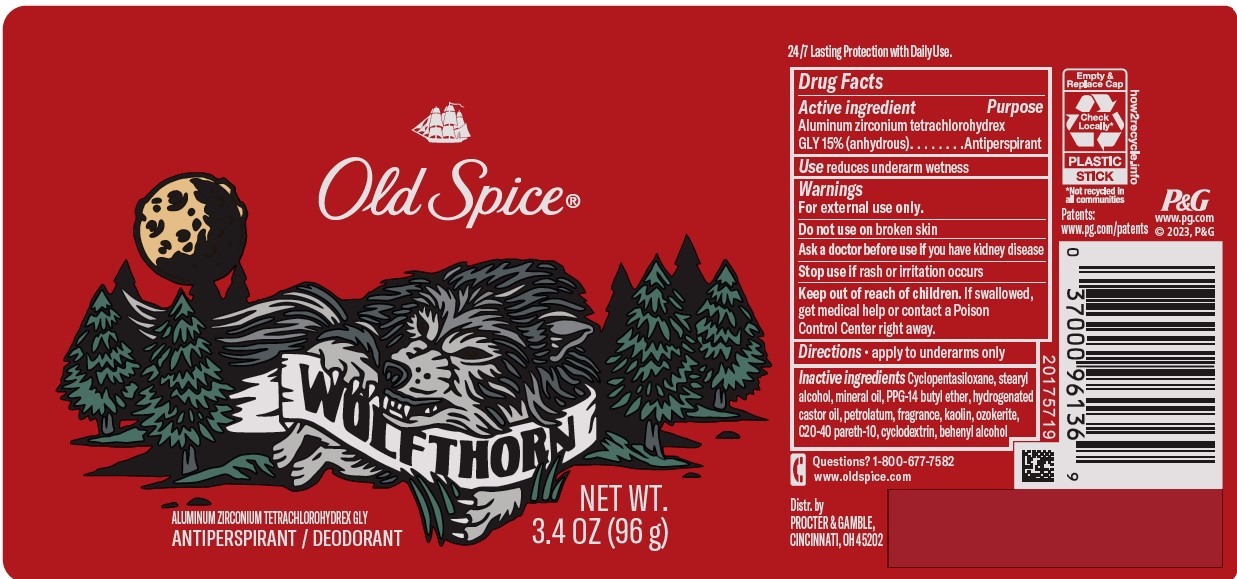 DRUG LABEL: Old Spice Wolfthorn
NDC: 69423-537 | Form: STICK
Manufacturer: The Procter & Gamble Manufacturing Company
Category: otc | Type: HUMAN OTC DRUG LABEL
Date: 20260128

ACTIVE INGREDIENTS: ALUMINUM ZIRCONIUM TETRACHLOROHYDREX GLY 15 g/100 g
INACTIVE INGREDIENTS: CERESIN; CYCLODEXTRINS; CYCLOPENTASILOXANE; STEARYL ALCOHOL; MINERAL OIL; KAOLIN; HYDROGENATED CASTOR OIL; PPG-14 BUTYL ETHER; C20-40 PARETH-10; BEHENYL ALCOHOL; PETROLATUM

Old Spice® Wolfthorn Invisible Solid

Drug Facts

Active ingredient

Aluminum zirconium tetrachlorohydrex Gly 15% (anhydrous)

Purpose

Antiperspirant

Use

reduces underarm wetness

Warnings

For external use only.

Do not use on broken skin

Ask a doctor before use if you have kidney disease

Stop use if rash or irritation occurs

Keep out of reach of children.
If swallowed, get medical help or contact a Poison Control Center right away.

Directions

- apply to underarms only

Inactive ingredients

Cyclopentasiloxane, stearyl alcohol, mineral oil, PPG-14 butyl ether, hydrogenated castor oil, petrolatum, fragrance, lkaolin, ozokerite, C20-40 pareth-10, cyclodextrin, behenyl alcohol

Questions?

1-800-677-7582

Dist. by PROCTER & GAMBLE,
CINCINNATI, OH 45202.

PRINCIPAL DISPLAY PANEL - 73 g Cylinder Label

Old Spice ®

Wolfthorn

ALUMINUM ZIRCONIUM

TETRACHLOROHYDREX GLY

ANTIPERSPIRANT/DEODORANT

NET WT. 2.6 OZ (73 g)